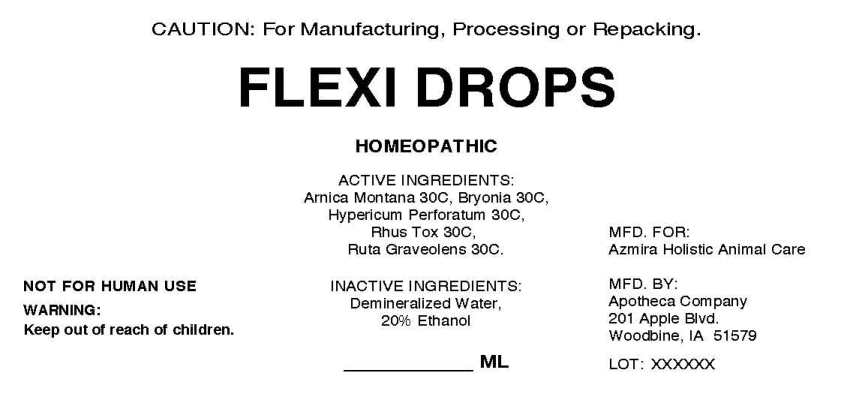 DRUG LABEL: Flexi Drops
NDC: 57520-1409 | Form: LIQUID
Manufacturer: Apotheca Company
Category: other | Type: BULK INGREDIENT - ANIMAL DRUG
Date: 20221027

ACTIVE INGREDIENTS: ARNICA MONTANA 30 [hp_C]/1 mL; BRYONIA ALBA ROOT 30 [hp_C]/1 mL; HYPERICUM PERFORATUM 30 [hp_C]/1 mL; TOXICODENDRON PUBESCENS LEAF 30 [hp_C]/1 mL; RUTA GRAVEOLENS FLOWERING TOP 30 [hp_C]/1 mL
INACTIVE INGREDIENTS: WATER; ALCOHOL

DRUG FACTS:

ACTIVE INGREDIENTS:

Arnica Montana 30C, Bryonia (Alba) 30C, Hypericum Perforatum 30C, Rhus Tox 30C, Ruta Graveolens 30C.

PURPOSE:

To be used for futher manufacturing, processing, or repacking.

WARNINGS:

NOT FOR HUMAN USE

Keep out of reach of children.

KEEP OUT OF REACH OF CHILDREN:

DOSAGE:

To be determined by final processor.

INDICATIONS:

To be determined by final processor.

INACTIVE INGREDIENTS:

Demineralized Water, 20% Ethanol.

QUESTIONS:

MFD. FOR:

Azmira Holistic Animal Care

MFD. BY:

Apotheca Company

201 Apple Blvd.

Woodbine, IA 51579

PACKAGE LABEL DISPLAY:

CAUTION: For Manufacturing, Processing, or Repacking.

FLEXI DROPS

HOMEOPATHIC

_________ ML